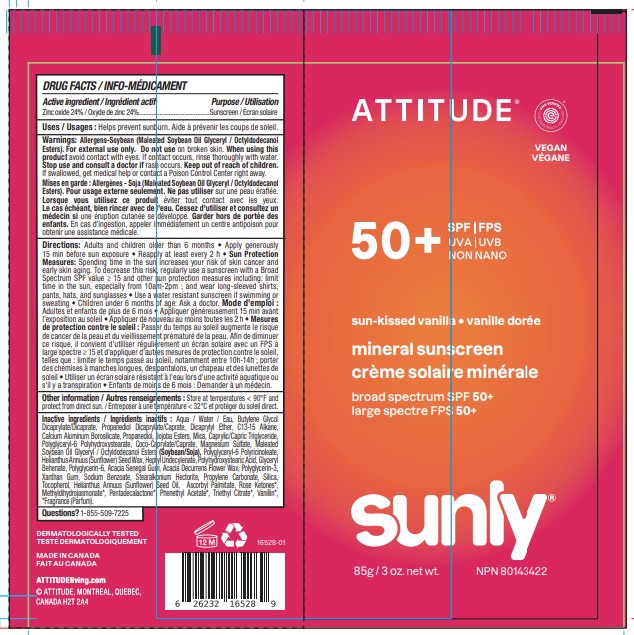 DRUG LABEL: ATTITUDE Sunly Mineral sunscreen SPF 50 Sun kissed vanilla
NDC: 61649-528 | Form: CREAM
Manufacturer: 9055-7588 Québec Inc.DBA ATTITUDE
Category: otc | Type: HUMAN OTC DRUG LABEL
Date: 20251128

ACTIVE INGREDIENTS: ZINC OXIDE 24 g/100 g
INACTIVE INGREDIENTS: TRIETHYL CITRATE; METHYLDIHYDROJASMONATE; HELIANTHUS ANNUUS SEED WAX; GLYCERYL DIBEHENATE; ACACIA SENEGAL GUM; POLYGLYCERYL-2 DIPOLYHYDROXYSTEARATE; POLYGLYCERYL-6 POLYRICINOLEATE; HEPTYL UNDECYLENATE; BUTYLENE GLYCOL DICAPRYLATE/DICAPRATE; CALCIUM ALUMINUM BOROSILICATE; POLYHYDROXYSTEARIC ACID (2300 MW); CAPRYLIC/CAPRIC TRIGLYCERIDE; TOCOPHEROL; HELIANTHUS ANNUUS (SUNFLOWER) SEED OIL; JOJOBA OIL; STEARALKONIUM HECTORITE; PROPYLENE CARBONATE; MALEATED SOYBEAN OIL GLYCERYL/OCTYLDODECANOL ESTERS; DICAPRYLYL ETHER; C13-15 ALKANE; AQUA; PROPANEDIOL DICAPRYLATE/CAPRATE; PROPANEDIOL; MICA; MAGNESIUM SULFATE; POLYGLYCERIN-6; ACACIA DECURRENS FLOWER WAX; POLYGLYCERIN-3; XANTHAN GUM; SODIUM BENZOATE; SILICA; ASCORBYL PALMITATE; COCO-CAPRYLATE/CAPRATE; .ALPHA.-DAMASCONE, (E)-; PENTADECALACTONE; PHENETHYL ACETATE

ATTITUDE Sunly Mineral sunscreen SPF 50 Sun-kissed vanilla

DRUG FACTS

ACTIVE INGREDIENT

Zinc oxide (24 %)

PURPOSE

Sunscreen

INDICATIONS AND USAGE

Helps prevent sunburn

WARNINGS

For external use only.

Do not use on broken skin.

When using this product avoid contact with eyes. If contact occurs, rinse thoroughly with water.

Keep out of reach of children. If swallowed, get medical help or contact a Poison Control Center right away.

Stop use and consult a doctor if rash occurs

OTHER SAFETY INFORMATION

Allergens-Soybean (Maleated Soybean Oil Glyceryl / Octyldodecanol Esters)

DOSAGE AND ADMINISTRATION

Adultds and children older than 6 months • Apply generously 15 min before sun exposure • Reapply at least every 2 h • Sun Protection Measures: Spending time in the sun increases your risk of skin cancer and early skin aging. To decrease this risk, regularly use a sunscreen with a Broad Spectrum SPF value ≥ 15 and other sun protection measures including: limit time in the sun, especially from 10am-2pm; and wear long-sleeved shirts, pants, hats, and sunglasses • Use a water resistant sunscreen if swimming or sweating • Children under 6 months of age: Ask a doctor.

INACTIVE INGREDIENT

Aqua / Water / Eau, Butylene Glycol Dicaprylate/Dicaprate, Propanediol Dicaprylate/Caprate, Dicaprylyl Ether, C13-15 Alkane, Calcium Aluminum Borosilicate, Propanediol, Jojoba Esters, Mica, Caprylic/Capric Triglyceride, Polyglyceryl-6 Polyhydroxystearate, Coco-Caprylate/Caprate, Magnesium Sulfate, Maleated Soybean Oil Glyceryl / Octyldodecanol Esters (Soybean/Soja), Polyglyceryl-6 Polyricinoleate, Helianthus Annuus (Sunflower) Seed Wax, Heptyl Undecylenate, Polyhydroxystearic Acid, Glyceryl Behenate, Polyglycerin-6, Acacia Senegal Gum, Acacia Decurrens Flower Wax, Polyglycerin-3, Xanthan Gum, Sodium Benzoate, Stearalkonium Hectorite, Propylene Carbonate, Silica, Tocopherol, Helianthus Annuus (Sunflower) Seed Oil, Ascorbyl Palmitate, Rose Ketones*, Methyldihydrojasmonate*, Pentadecalactone*, Phenethyl Acetate*, Triethyl Citrate*, Vanillin*, *Fragrance (Parfum).

STORAGE AND HANDLING

Store at temperatures < 90F and protect from direct sun.

Questions ? 1-855-509-7225

PACKAGE LABEL

ATTITUDE

EWG Verified

VEGAN

SPF 50+

UVA ¦ UVB

NON NANO

Sun-kissed vanilla

mineral sunscreen

Broad spectrum SPF 50+

sunly

85g / 3 oz. net wt.

NPN 80143422

Made in Canada

Dermatologically tested